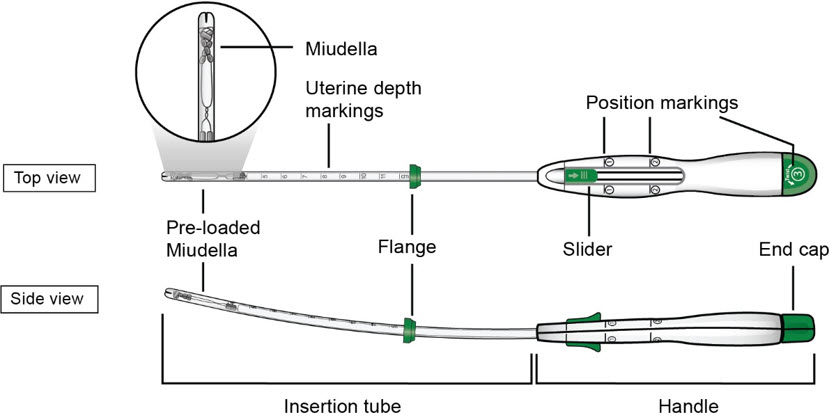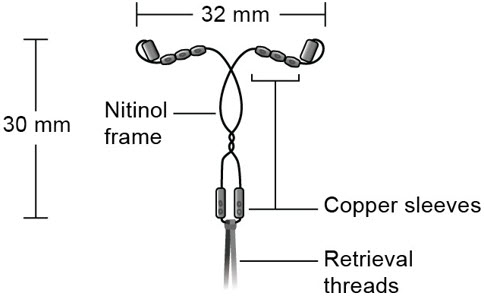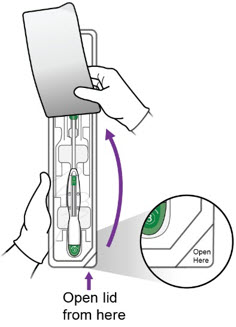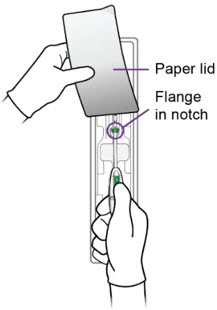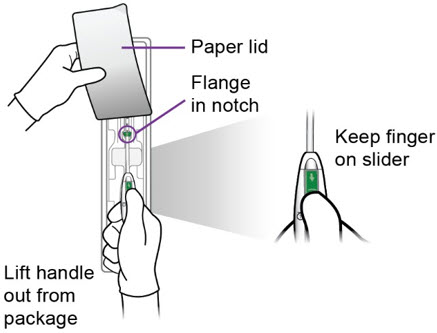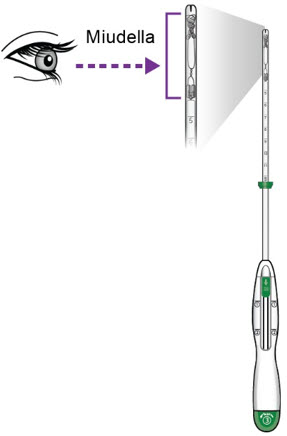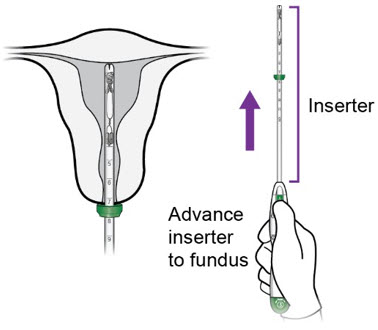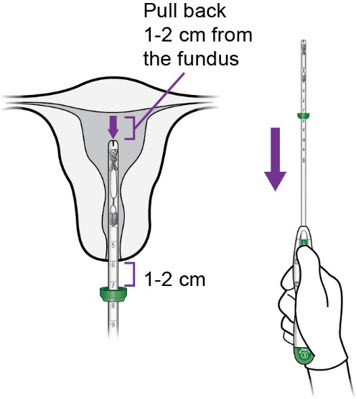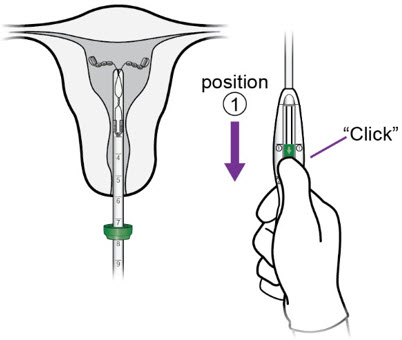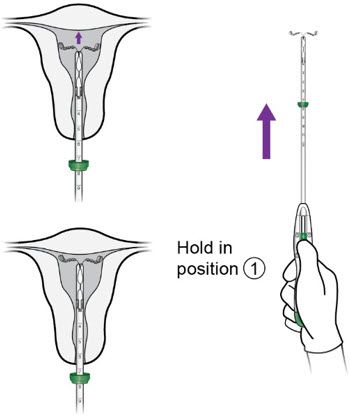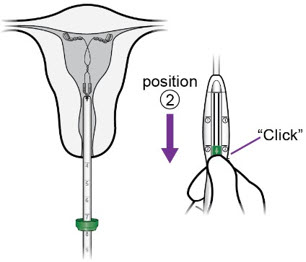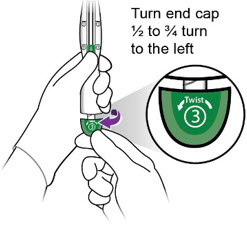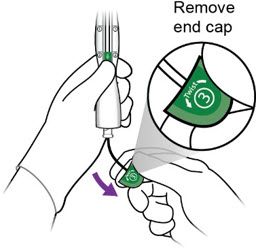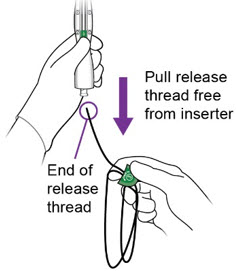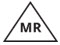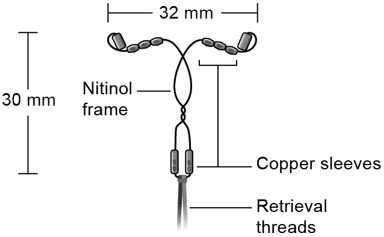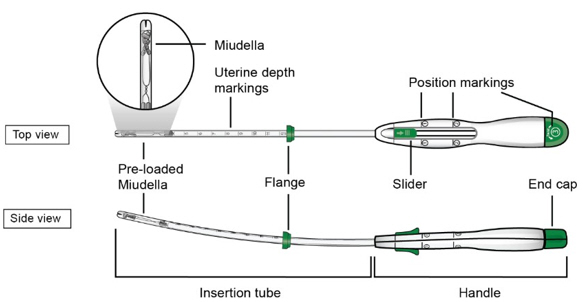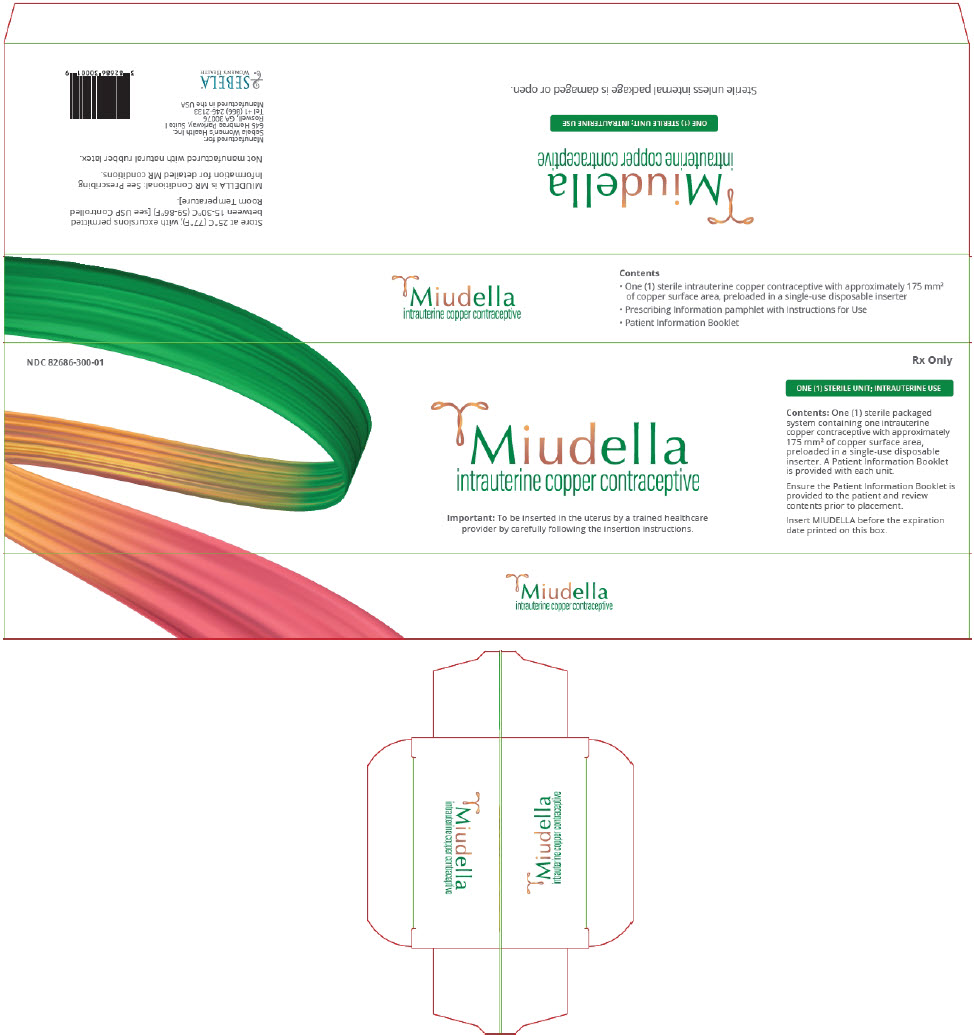 DRUG LABEL: Miudella
NDC: 82686-300 | Form: INTRAUTERINE DEVICE
Manufacturer: Sebela Women's Health Inc.
Category: prescription | Type: HUMAN PRESCRIPTION DRUG LABEL
Date: 20250609

ACTIVE INGREDIENTS: COPPER 175 mm/1 1

HIGHLIGHTS OF PRESCRIBING INFORMATION

These highlights do not include all the information needed to use MIUDELLA®safely and effectively. See full prescribing information for MIUDELLA.
MIUDELLA®(copper intrauterine system)
Initial U.S. Approval: 1984

WARNING: RISK OF COMPLICATIONS DUE TO IMPROPER INSERTION

- Improper insertion of intrauterine systems, including Miudella, increases the risk of complications [see Warnings and Precautions (5.1)].
- Proper training prior to first use of Miudella can minimize the risk of improper Miudella insertion [see Warnings and Precautions (5.1)].
- Miudella is available only through a restricted program under a Risk Evaluation and Mitigation Strategy (REMS) called the Miudella REMS program to ensure healthcare providers are trained on the proper insertion of Miudella prior to first use [see Warnings and Precautions (5.2)].

1 INDICATIONS AND USAGE

Miudella is a copper-containing intrauterine system (IUS) indicated for prevention of pregnancy in females of reproductive potential for up to 3 years.(1)

2 DOSAGE AND ADMINISTRATION

- Insert a single Miudella at the fundus of the uterine cavity. Miudella must be removed or replaced after 3 years. (2.1)
- Insert Miudella only if you are a trained healthcare provider using clean technique. Follow insertion instructions exactly as described. (2.1)
- See the Full Prescribing Information for recommended timing of insertion, preparation instructions, insertion procedures, postplacement management, and instructions on removing Miudella. (2.2, 2.3, 2.4, 2.5, 2.6)
- Patient can be re-examined as clinically indicated.

3 DOSAGE FORMS AND STRENGTHS

Intrauterine system: 175 mm^2exposed copper surface area. Miudella has a nitinol frame with copper sleeves and monofilament polymer retrieval thread, preloaded in a sterile inserter.(3, 16)

4 CONTRAINDICATIONS

- Pregnancy or suspicion of pregnancy. (4)
- Uterine anomaly that distorts the uterine cavity and would be incompatible with correct IUS placement. (4)
- Acute pelvic inflammatory disease (PID) (4)
- Postpartum endometritis or postabortal endometritis in past 3 months. (4)
- Known or suspected uterine or cervical malignancy (4)
- For use as post-coital contraception (emergency contraception) (4)
- Uterine bleeding of unknown etiology (4)
- Untreated acute cervicitis or vaginitis or other lower genital tract infection (4)
- Conditions associated with increased susceptibility to pelvic infections (4)
- Wilson's disease (4)
- A previously placed IUS that has not been removed (4)
- Hypersensitivity to any component of Miudella including copper, nitinol or any trace elements present in the copper components of Miudella (4)

5 WARNINGS AND PRECAUTIONS

- Risk of Ectopic Pregnancy: Promptly evaluate females who become pregnant for ectopic pregnancy while using Miudella. (5.3)
- Risks with Intrauterine Pregnancy: Increased risk of spontaneous abortion, septic abortion, premature delivery, sepsis, septic shock, and death if pregnancy occurs. Remove Miudella if pregnancy occurs with Miudella in place. (5.4)
- Sepsis: Group A streptococcal infection has been reported; strict aseptic technique is essential during insertion. (5.5)
- Pelvic Inflammatory Disease (PID): Promptly evaluate patients with complaints of fever or abdominal pain after insertion of Miudella. (5.6)
- Perforation resulting in embedment or translocation: May reduce contraceptive effectiveness and require surgery. Risk is increased if inserted in postpartum and lactating females and may be increased if inserted in females with fixed, retroverted uteri or noninvoluted uteri. (5.7)
- Expulsion: Partial or complete expulsion may occur. Remove a partially expelled Miudella. (5.8)
- Bleeding patterns: May be altered and result in heavier and longer bleeding with spotting. (5.10)
- MRI Safety Information: Patients using Miudella can be safely scanned with MRI only under certain conditions. (5.11)

6 ADVERSE REACTIONS

Most common adverse reactions (incidence ≥ 5%) are: heavy menstrual bleeding, dysmenorrhea, intermenstrual bleeding, pelvic discomfort, procedural pain, pelvic pain, post procedural hemorrhage, dyspareunia. (6.1)

To report SUSPECTED ADVERSE REACTIONS, contact Sebela Women's Health Inc. at 1-866-246-2133 or FDA at 1-800-FDA-1088 or www.fda.gov/medwatch.

FULL PRESCRIBING INFORMATION

WARNING: RISK OF COMPLICATIONS DUE TO IMPROPER INSERTION

- Improper insertion of intrauterine systems, including Miudella, increases the risk of complications [see Warnings and Precautions (5.1)] .
- Proper training prior to first use of Miudella can minimize the risk of improper Miudella insertion [see Warnings and Precautions (5.1)].
- Miudella is available only through a restricted program under a Risk Evaluation and Mitigation Strategy (REMS) called the Miudella REMS program to ensure healthcare providers are trained on the proper insertion of Miudella prior to first use [see Warnings and Precautions (5.2)].

1 INDICATIONS AND USAGE

Miudella is indicated for prevention of pregnancy in females of reproductive potential for up to 3 years.

2 DOSAGE AND ADMINISTRATION

2.1 Important Dosage and Administration Instructions

- Miudella is supplied sterile in a sealed package with a sterile single use inserter for placement. Do not open the package until required for insertion. Do not use if the seal of the sterile package is broken or appears compromised.
- Before considering use of Miudella, make sure that the patient is an appropriate candidate for Miudella. Exclude pregnancy (consider the possibility of ovulation and conception) prior to use [see Contraindications (4)and Warnings and Precautions (5)].
- Only a healthcare provider should insert Miudella. Healthcare providers should be thoroughly familiar with the product, product educational materials, product insertion instructions, and prescribing information before inserting Miudella.
- The IUS is provided preloaded in the inserter (see Figure A).
- Remove Miudella on or before 3 years from the date of insertion.
- Replace Miudella at the time of removal with a new Miudella if continued contraceptive protection is desired.

FigureA : Miudella Intrauterine System (IUS) Preloaded Inserter

- Figure B: Detailed diagram of Miudella

2.2 Timing of Insertion

- Miudella can be inserted at any time during the menstrual cycle. If switching to Miudella from another contraceptive, discontinue the previous method (see Table 1).

• Table 1: Recommended Timing of Miudella Insertion
Clinical Scenario | Recommended Timing of Miudella Insertion
- Start Miudella in females not currently using contraception | At any time during the menstrual cycle.
- Switch to Miudella from an oral, transdermal, or vaginal form of hormonal contraception or an injectable progestin contraceptive | At any time during the menstrual cycle; discontinue the previous method.
- Switch to Miudella from a contraceptive implant or other intrauterine system | Same day the implant or IUS is removed (insert at any time during the menstrual cycle).

2.3 Preparation for Insertion

1. Ensure use of clean technique during the procedure.
2. Perform a bimanual exam to establish the size, shape, and position of the uterus and to rule out abnormalities that would preclude safe placement of Miudella.
3. Gently insert a speculum to visualize the cervix.
4. Thoroughly cleanse the cervix with chlorhexidine or povidone-iodine.
5. Apply a sterile tenaculum to the cervix. Apply traction with the tenaculum. Gently advance a sterile uterine sound to the fundus. Note any uterine anomaly and the depth in centimeters.

2.4 Insertion Procedure

Step 1 – Open the Sterile Package
1. Remove the sterile packaging containing Miudella from the box. 2. Inspect the packaging to confirm a sterile barrier is maintained. Do not use if the packaging is not intact or there are concerns of compromised sterility.
1. Peel back the paper lid ¾ of the way up the package to expose the inserter handle and flange. |  | c.
• Step 2 – Setting the Flange
1. Grasp the handle while maintaining your thumb or forefinger on the slider to restrict its movement. Gently lift the handle from the package, taking care not to bend or kink the insertion tube. Use the paper lid to hold the flange in the notch of the package, slowly pull the handle back, while keeping the flange in the notch, until the flange is set to the desired depth measured during sounding. Alternately, set the flange with sterile gloves after you have lifted the inserter out of the packaging. 2. After setting the flange, remove the inserter from the package. |  | a.
1. Inspect the end of the inserter to confirm that Miudella is positioned as shown. |  | c.
• Step 3 – Inserter Placement
1. Continue applying upward pressure with the thumb/forefinger on the slider to avoid early deployment of the IUS. Maintain traction with the tenaculum and gently advance the inserter through the cervical canal. Progress slowly towards the fundus until the flange is at the level of the external cervical os and the tip of the inserter is at the fundus.; - CAUTION: Do not advance the flange beyond the external os, as this may result in fundal perforation. - NOTE: Do not force the inserter into the external or internal cervical os. If necessary, consider use of an os finder or a small cervical dilator. |  | a.
Step 4 -Miudella Placement
1. Once the flange is at the level of the external os, gently withdraw the inserter back towards you 1–2 cm. |  | a.
1. With the inserter tip 1-2 cm from the fundus (i.e., with the flange 1-2 cm from the os), move the slider to position ①. |  | b.
1. Holding the slider securely in position ①, slowly re-advance the inserter until you feel the fundus. |  | c.
1. With the IUS at the fundus, hold the inserter steady and move the slider to position ②. |  | d.
1. Release Miudella from the inserter: 1. Hold the inserter handle steady with one hand and grasp the end cap with the other hand.
1. 1. While holding the inserter steady with one hand, twist the green end cap (labeled ③) ½ - ¾ turn to the left with the other hand.
1. 1. Remove end cap. One end of the white release thread is attached to the end cap as shown in the diagram and removing the end cap initiates removal of the release thread. |  | iii.
1. 1. Completelyremove the white release thread from the inserter until you see the free end of the thread - Do not cut the white release thread. The length of the release thread is approximately twice the length of the inserter. |  | iv.
1. Slowly remove the inserter from the cervix and vaginal cavity and properly dispose of the inserter and end cap with release thread.

- Step 5 – Confirm the Retrieval Thread Ends
  1. Confirm that the blue retrieval thread ends are visible past the external os. The retrieval thread ends are pre-cut to typically allow 3-4 cm of exposed thread in the vaginal cavity without the need for trimming, and hence cutting of excess thread length is generally not required.
  2. Should additional trimming of the thread ends be desired, cut the thread ends perpendicular to the thread length, for example, with sterile curved scissors, leaving the desired amount of visible length outside the cervix.
  3. Remove the tenaculum and achieve adequate hemostasis.
  4. Remove speculum from the vaginal cavity.
  5. Miudella placement is now complete.
- Important information to consider during and after placement:
  - If you suspect that Miudella is not in the correct position, check placement (for example, with transvaginal ultrasound). Remove Miudella if it is not positioned completely within the uterus. A removed Miudella must not be reused.
  - If there is clinical concern and/or exceptional pain or bleeding during or after placement, conduct appropriate and timely measures and assessments. For example, ultrasound should be performed to exclude perforation, embedment, or translocation.

2.5 Post-placement Management of Miudella

Following placement:

- Examine the female after her first menses to confirm that Miudella is still in place. You should be able to visualize or feel only the threads. The length of the visible threads may change with time. However, no action is needed unless you suspect partial expulsion, perforation, pregnancy, or breakage.
- If you cannot find the threads in the vagina, check that Miudella is still in the uterus. The threads can retract into the uterus or break, or Miudella can break, perforate the uterus, or be expelled. Gentle probing of the cavity, x-ray, or sonography may be required to locate Miudella.
- Remove Miudella if it has been partially expelled or perforated the uterus [see Warnings and Precautions (5.7, 5.8)].

2.6 Removal of Miudella

Timing of Removal

- Miudella can be removed at any time prior to 3 years after insertion.
- Remove Miudella no later than 3 years after insertion. After removal, a new Miudella can be inserted.
- If the threads are not visible, determine location of Miudella by ultrasound.
- If pregnancy is not desired, and the patient is not having a new IUS or implant placed that day, the removal should be carried out during the first 7 days of the menstrual cycle, provided the woman is experiencing regular menses. If the patient is not having a new IUS or implant placed that day and removal will occur at other times during the cycle or the woman does not experience regular menses, she is at risk of pregnancy: start a new contraceptive method a week prior to removal for these women.

Removal Instructions

1. Use a speculum and visualize the cervix.
2. Remove Miudella with forceps, pulling gently on the exposed threads. The flexible arms of Miudella will fold upwards as it is withdrawn from the uterus. If the threads are not visible, determine location of Miudella by ultrasound.
3. If Miudella is found to be in the uterine cavity on an ultrasound exam, it may be removed using a narrow forceps, such as an alligator forceps. Consider use of local anesthetic for a paracervical block if cervical dilation is required. After removal of Miudella, examine the system to ensure that it is intact.
4. Removal may be associated with some pain and/or bleeding or vasovagal reactions (e.g. syncope, bradycardia, seizures) especially in patients with a predisposition to these conditions.

3 DOSAGE FORMS AND STRENGTHS

Intrauterine system: 175 mm^2exposed copper surface area. Miudella is a copper-containing IUS that has a flexible nitinol frame with copper sleeves and monofilament polymer retrieval thread, preloaded in a sterile inserter with a tapered rounded tip and packaged in a sealed tray with lid.

4 CONTRAINDICATIONS

The use of Miudella is contraindicated when one or more of the following conditions exist:

- Pregnancy or suspicion of pregnancy [see Warnings and Precautions (5.4)and Use in Specific Populations (8.1)]
- Congenital or acquired abnormalities of the uterus, including leiomyomas, resulting in distortion of the uterine cavity
- Acute pelvic inflammatory disease (PID) [see Warnings and Precautions (5.6)]
- Postpartum endometritis or postabortal endometritis in the past 3 months. [see Warnings and Precautions (5.6)]
- Known or suspected uterine or cervical malignancy
- For use as post-coital contraception (emergency contraception)
- Uterine bleeding of unknown etiology
- Untreated acute cervicitis or vaginitis or other lower genital tract infection
- Conditions associated with increased susceptibility to pelvic infections [see Warnings and Precautions (5.6)]
- Wilson's disease [see Warnings and Precautions (5.9)]
- A previously placed IUS that has not been removed
- Hypersensitivity to any component of Miudella including to polypropylene, copper, nitinol, an alloy of nickel and titanium, or any of the trace elements present in the copper component of Miudella [see Adverse Reactions (6)and Description (11)] . Persons with allergic reactions to these components may suffer an allergic reaction to this intrauterine system. Prior to placement, patients should be counseled on the materials contained in the IUS, as well as potential for allergy/hypersensitivity to these materials.

5 WARNINGS AND PRECAUTIONS

5.1 Risk of Complications Due to Improper Insertion

Improper insertion of intrauterine systems, including Miudella, increases the risk of perforation, infection, undiagnosed abnormal bleeding, pregnancy loss (if pregnancy occurs with IUS in situ), and expulsion.

Proper training prior to first use of Miudella can minimize the risk of improper insertion. Miudella is available only through a restricted program under a REMS [see Warnings and Precautions (5.2)].

5.2 Miudella REMS

Miudella is only available through a restricted program under a REMS called Miudella REMS Programto ensure healthcare providers are trained prior to first use [see Warnings and Precautions (5.1)]. Notable requirements include the following:

- Healthcare providers must be certified with the program by enrolling and completing training on the proper insertion of Miudella prior to first use [see Warnings and Precautions (5.2)].
- Pharmacies and healthcare settings that dispense Miudella must be certified by enrolling in the REMS and must only dispense Miudella to certified healthcare providers.

Further information is available at miudellarems.com and 1-855-337-0772.

5.3 Risk of Ectopic Pregnancy

Evaluate for possible ectopic pregnancy in any female who becomes pregnant while using Miudella because a pregnancy that occurs with Miudella in place is more likely to be ectopic than a pregnancy in the general population. However, because Miudella prevents most pregnancies, females who use Miudella have a lower risk of an ectopic pregnancy than sexually active females who do not use any contraception.

The incidence of ectopic pregnancy in the clinical trials with Miudella was approximately 0.3%. Ectopic pregnancy may require surgery and may result in loss of fertility.

Patients who use Miudella should be informed about recognizing the signs and symptoms of ectopic pregnancy and promptly reporting them to their healthcare professional, and about the associated risks of ectopic pregnancy (e.g., loss of fertility).

5.4 Risks with Intrauterine Pregnancy

If intrauterine pregnancy occurs with Miudella in place and the thread ends are visible or can be retrieved from the cervical canal, remove Miudella. Leaving it in place may increase the risk of spontaneous abortion and preterm labor. Removal of Miudella may also result in spontaneous abortion. In the event of an intrauterine pregnancy with Miudella, consider the following:

Septic Abortion

In females becoming pregnant with an intrauterine system (IUS), including Miudella in place, septic abortion, with septicemia, septic shock, and death, may occur. Septic abortion typically requires hospitalization and treatment with intravenous antibiotics. Septic abortion may result in spontaneous abortion or a medical indication for pregnancy termination. A hysterectomy may be required if severe infection of the uterus occurs, which will result in permanent infertility.

Continuation of Pregnancy

If a female becomes pregnant with Miudella in place and if Miudella cannot be removed or the female chooses not to have it removed, warn her that failure to remove Miudella increases the risk of miscarriage, sepsis, premature labor, and premature delivery. Prenatal care should include counseling about these risks and that she should report immediately any flu-like symptoms, fever, chills, cramping, pain, bleeding, vaginal discharge or leakage of fluid, or any other symptom that suggests complications of the pregnancy.

5.5 Sepsis

Severe infection or sepsis, including Group A streptococcal sepsis (GAS), have been reported following insertion of IUSs. In some cases, severe pain occurred within hours of insertion followed by sepsis within days. Because death from GAS is more likely if treatment is delayed, it is important to be aware of these rare but serious infections. Aseptic technique during insertion of Miudella is essential to minimize serious infections such as GAS.

5.6 Pelvic Infection

Promptly examine users with complaints of lower abdominal or pelvic pain, odorous discharge, unexplained bleeding, fever, genital lesions or sores. Remove Miudella in cases of recurrent pelvic inflammatory disease or endometritis, or if an acute pelvic infection is severe or does not respond to treatment.

Pelvic Inflammatory Disease (PID)

Miudella is contraindicated in the presence of known or suspected PID or endometritis [see Contraindications (4)] . IUSs have been associated with an increased risk of PID, most likely due to organisms being introduced into the uterus during insertion.

Females at increased risk for PID

PID is often associated with a sexually transmitted infection (STI), and Miudella does not protect against STI. The risk of PID is greater for females who have multiple sexual partners, and also for females whose sexual partner(s) have multiple sexual partners. Females who have had PID are at increased risk for a recurrence or re-infection. In particular, ascertain whether the female is at increased risk of infection (for example, leukemia, acquired immune deficiency syndrome [AIDS], intravenous drug abuse).

Subclinical PID

PID may be asymptomatic but still result in tubal damage and its sequelae.

Treatment of PID

Following a diagnosis of PID, or suspected PID, bacteriologic specimens should be obtained and antibiotic therapy should be initiated promptly. Removal of Miudella after initiation of antibiotic therapy is appropriate in cases of recurrent PID or endometritis, or if an acute pelvic infection is severe or does not respond to treatment.

Actinomycosis

Actinomycosis has been associated with IUS use. Symptomatic patients with known actinomycosis infection should have Miudella removed and receive antibiotics. Actinomycetes can be found in the genital tract cultures in healthy patients without IUSs. The significance of actinomyces-like organisms on Pap test in an asymptomatic IUS user is unknown, and so this finding alone does not always require Miudella removal and treatment. When possible, confirm a Pap test diagnosis with cultures.

5.7 Perforation

Partial or total perforation of the uterine wall or cervix may occur during insertions, although the perforation may not be detected until sometime later. Perforation may also occur at any time during IUS use. Perforation that results in embedment or translocation may reduce contraceptive efficacy and result in pregnancy. The incidence of perforation during or following Miudella insertion in clinical trials was 0.1% (2 out of 1904).

A post-marketing safety study conducted in Europe (EURAS IUS) with IUSs, including copper IUSs, demonstrated an increased risk of perforation in postpartum and lactating women. The risk of perforation may be increased if an IUS, such as Miudella, is inserted when the uterus is fixed, retroverted or not completely involuted during the postpartum period.

If perforation is suspected or if known perforation occurs during placement, the IUS should be removed as soon as possible. Surgery may be required. Preoperative imaging followed by laparoscopy or laparotomy may be required to remove the IUS from the peritoneal cavity. Delayed detection or removal of Miudella in cases of perforation may result in migration outside the uterine cavity, adhesions, peritonitis, intestinal penetration, intestinal obstruction, abscesses and/or damage to adjacent organs.

5.8 Expulsion

Partial or complete expulsion of Miudella has been reported, resulting in the loss of contraceptive protection. The incidence of expulsion in the clinical trials with Miudella was 3.6% through 3 years of use. Consider further diagnostic imaging, such as x-ray, to confirm expulsion if the IUS is not found in the uterus on ultrasound.

Miudella should be placed no earlier than 4 weeks post-pregnancy to mitigate the risk of expulsion that may be increased when the uterus is not completely involuted at the time of insertion. Remove a partially expelled Miudella and do not attempt to push a partially expelled Miudella into the uterus. If expulsion has occurred, a new Miudella may be inserted when there is reasonable certainty the patient is not pregnant.

5.9 Wilson's Disease

Miudella may exacerbate Wilson's disease, a rare genetic disease affecting copper excretion; therefore, the use of Miudella is contraindicated in females with Wilson's disease [see Contraindications (4)] .

5.10 Bleeding Pattern Alterations

Miudella can alter the bleeding pattern and result in heavier and longer menstrual cycles with intermenstrual spotting.

In three clinical trials with Miudella [see Adverse Reactions (6.1)] , menstrual changes were the most common medical reason for discontinuation. Discontinuation rates for pain and bleeding combined were highest in the first year of use and diminished thereafter. The percentage of females who discontinued Miudella because of bleeding problems or pain during this study ranged from 8.5% in the first year to 3.2% in Year 3. Females complaining of heavy vaginal bleeding should be evaluated and treated, and may need to discontinue Miudella [see Adverse Reactions (6.1)] .

5.11 Magnetic Resonance Imaging (MRI) Safety Information

MRI Safety Information MR Conditional | The Miudella Intrauterine Device (IUD)is MR Conditional. A patient with Miudellamay be safely scanned under the following conditions. Failure to follow these conditions may result in injury to the patient.
Nominal Values of Static Magnetic Field (T) |  | 1.5-Tesla or 3.0-Tesla
Maximum Spatial Field Gradient |  | 40 T/m (4,000 gauss/cm)
Type of RF Excitation |  | Circularly Polarized (CP) (i.e., Quadrature-Transmission)
Transmit RF Coil Information |  | There are no transmit RF coil restrictions. Accordingly, the following may be used: body transmit RF coil and all other RF coil combinations (i.e., body RF coil combined with any receive-only RF coil, transmit/receive head RF coil, transmit/receive knee RF coil, etc.)
Operating Mode |  | Normal Operating Mode
Maximum Whole-Body Averaged SAR |  | 2 W/kg (Normal Operating Mode)
Limits on Scan Duration |  | 2 W/kg whole body average SAR for 60 minutes of continuous RF exposure (a sequence or back to back sequences/series without breaks)
MR Image Artifact |  | The presence of this implant produces an imaging artifact. In testing with gradient-echo sequencing, the shape of the image artifact follows the approximate contour of the device and extends radially up to 0.7 cm from the device.

5.12 Medical Diathermy

Medical equipment that contains high levels of Radiofrequency (RF) energy such as diathermy may cause health effects (by heating tissue) in females with a metal-containing IUS including Miudella. Avoid using high medical RF transmitter devices in females with Miudella.

6 ADVERSE REACTIONS

The following serious adverse reactions are discussed elsewhere in the labeling:

- Ectopic pregnancy [see Warnings and Precautions (5.3)]
- Intrauterine pregnancy [see Warnings and Precautions (5.4)]
- Sepsis [see Warnings and Precautions (5.5)]
- Pelvic Infection [see Warnings and Precautions (5.6)]
- Perforation [see Warnings and Precautions (5.7)]
- Expulsion [see Warnings and Precautions (5.8)]
- Wilson's Diseas e [see Warnings and Precautions (5.9)]
- Bleeding Pattern Alteration [see Warnings and Precautions (5.10)]

6.1 Clinical Trials Experience

Because clinical trials are conducted under widely varying conditions, adverse reaction rates observed in the clinical trials of a drug cannot be directly compared to rates in the clinical trials of another drug and may not reflect the rates observed in clinical practice.

The data described below reflect exposure of 1,904 healthy 17- to 45-year-old women (mean age 27.5 ± 5.72 years) to Miudella. These data come from two multi-center contraceptive trials with a 3-year duration and a single, multi-center comparative bioavailability study with a 3 year duration, all conducted in the United States, enrolling generally healthy, postmenarcheal females to 45 years old. In total 1,904 subjects were exposed to Miudella for one year and 916 completed three years. The data in these trials cover approximately 51,692 cycles of exposure.

The following adverse reactions have been observed in ≥5% of users in clinical trials with Miudella: heavy menstrual bleeding, dysmenorrhea, intermenstrual bleeding, pelvic discomfort, procedural pain, pelvic pain, post procedural hemorrhage, and dyspareunia.

Table 2 shows discontinuation rates from the 3 multi-center clinical studies by adverse reaction and year.

• Table 2: Summary of Rates [Rates were calculated by weighting the annual rates by the number of subjects starting each year.] (No. per 100 Subjects) by Year for Adverse Reactions Causing Discontinuation
 | Year
 | 1 | 2 | 3
Number of Women at Start of Year | 1,904 | 1,463 | 1,118
Bleeding/Pain [Bleeding/Pain includes the preferred terms (PTs) Abdominal pain, Abdominal pain lower, Post procedural discomfort, Procedural pain, Coital bleeding, Dysmenorrhea, Dyspareunia, Heavy menstrual bleeding, Intermenstrual bleeding, Menometrorrhagia, Pelvic discomfort, Pelvic pain, Polymenorrhea, Uterine hemorrhage, Uterine spasm] | 8.5 | 5.1 | 3.2
Expulsion | 1.9 | 1.0 | 0.9
Other Medical Event [Includes PTs embedded device (n=6) and uterine perforation (n=1)] | 0.2 | 0.1 | 0.3

According to the safety analyses of these three studies, it was determined the incidence of expulsion of Miudella did not vary significantly by body mass index (BMI). There was no statistically significant difference in the incidence of expulsion of Miudella in normal weight versus obese females.

8 USE IN SPECIFIC POPULATIONS

8.1 Pregnancy

Risk Summary

Use of Miudella is contraindicated for use in pregnant females because there is no need for pregnancy prevention in a female who is already pregnant and Miudella may cause adverse pregnancy outcomes. If a female becomes pregnant with Miudella in place, there is an increased risk of miscarriage, sepsis, premature labor, and premature delivery [see Contraindications (4)and Warnings and Precautions (5.3, 5.4)] . Advise the female of the potential risks if pregnancy occurs with Miudella in place.

Published studies on pregnancy outcomes exposed to copper IUSs report up to 27% miscarriage when the IUS was removed compared to 77% miscarriage when the IUS remained in the uterus. Studies on Miudella and birth defects have not been conducted.

8.2 Lactation

Risk Summary

No difference has been detected in concentration of copper in human milk before and after insertion of copper IUSs, such as Miudella. There is no information on the effect of copper in a breastfed child or the effect on milk production. The developmental and health benefits of breastfeeding should be considered along with the mother's clinical need for Miudella and any potential adverse effects on the breastfed child from Miudella.

8.3 Females and Males of Reproductive Potential

Return to Fertility After Discontinuing Miudella

In Study 1 (NCT03633799), return to fertility was investigated in a total of 63 women who desired pregnancy after study discontinuation and provided follow-up information. The probability to conceive within 12 months after removal of Miudella was 74.1% [see Clinical Studies (14)].

8.4 Pediatric Use

The safety and effectiveness of Miudella have been established in females of reproductive potential. Efficacy is expected to be the same for postmenarcheal females regardless of age. Miudella is not indicated in females before menarche.

8.5 Geriatric Use

Miudella has not been studied in women over 65 years of age and is not indicated in this population.

11 DESCRIPTION

11.1 Miudella

Miudella (copper intrauterine system) contains 99.99% pure copper for use as a contraceptive. Copper (Cu) has a molecular weight of 63.546 g/mol. Miudella consists of ten copper sleeves attached to a flexible nitinol (nickel-titanium alloy) frame measuring 32 mm horizontally and 30 mm vertically, and a polypropylene monofilament retrieval thread tied to the vertical stem. Miudella has a total exposed copper surface area of 175 mm^2and is provided sterile and preloaded in an inserter.

- Figure C: Diagram of Miudella

11.2 Inserter

The inserter device provided with Miudella is a single use, disposable, sterile insertion system (insertion tube with a tapered rounded tip, depth markings and flange, and handle with slider and endcap); preloaded with the IUS for intrauterine administration. Once Miudella has been inserted, the inserter is discarded.

Figure D: Diagram of Inserter

12 CLINICAL PHARMACOLOGY

12.1 Mechanism of Action

Copper continuously released into the uterine cavity contributes to the contraceptive effectiveness of Miudella. Mechanism(s) by which copper enhances contraceptive efficacy include interference with sperm transport and fertilization of an egg.

12.2 Pharmacodynamics

The exposure-response relationship and time course of pharmacodynamic response for the safety and effectiveness of Miudella have not been fully characterized.

12.3 Pharmacokinetics

The pharmacokinetics (PK) of copper following insertion of Miudella were investigated in 20 healthy premenopausal female adult subjects. Table 3 shows PK parameters of serum copper with or without baseline-adjustment following 57 days after insertion, and serum copper concentrations during 3 years after insertion.

• Table 3: PK parameters and copper concentrations after Miudella insertion
 | Parameters | Mean (standard deviation)
 | Parameters | No adjustment | Baseline-adjusted
PK parameters | Cmax, Day1-57(ng/mL) | 1210 (202) | 63.5 (84.1)
PK parameters | AUCDay1-57(day×ng/mL) | 59700 (8310) | 992 (1680)
PK parameters | CYear1(ng/mL) | 965 (197) | 7.5 (19.4)
PK parameters | CYear2(ng/mL) | 1020 (168) | 25.7 (48.7)
PK parameters | CYear3(ng/mL) | 986 (148) | 17.2 (43.0)
Cmax: peak concentration
C: concentration
AUC: area under the serum concentration-time curve

13 NONCLINICAL TOXICOLOGY

13.1 Carcinogenicity, Mutagenicity, Impairment of Fertility

Adequate long-term studies in animals to assess the carcinogenic potential of a copper-containing IUS have not been performed.

A chemical characterization and toxicological risk assessment of the extractables derived from the copper-containing IUS were utilized to address carcinogenicity, mutagenicity and reproductive/developmental toxicity risks. The toxicological risk assessment indicates that the risks of carcinogenicity, mutagenicity and reproductive/developmental toxicity caused by the copper-containing IUS are negligible.

14 CLINICAL STUDIES

The efficacy of Miudella for the prevention of pregnancy in women of reproductive potential for up to 3 years was demonstrated in Study 1 (NCT03633799), a multi-center, single-arm, open-label study conducted in the U.S. Women were excluded if they were less than six weeks postpartum, had a history of previous IUS complications, were known to be HIV positive, or were otherwise at high risk for sexually transmitted infections. There were no exclusions based on BMI.

Study 1 included 1601 generally healthy women aged 17 to 45 years who had Miudella successfully placed. Of these 60% (960/1601) were nulliparous. Successful placement of Miudella with first attempt occurred in 96% of the subjects and 99% with two insertion attempts by healthcare providers who received training on proper insertion prior to first use. The median age was 27 years, the mean weight was 75.3 kg (range 40.6 kg to 170.1 kg); mean BMI was 27.9 kg/m^2(range 15.8 kg/m^2to 63.5 kg/m^2); 74% were White, 15% were Black, 5% were Asian, and 6% were Other; 19% were Hispanic.

The primary endpoint for Study 1 was the contraceptive efficacy of Miudella through 3 years of use as measured by the Pearl Index (PI) in women 17 to 35 years of age. The PI was calculated based on 28-day equivalent exposure cycles; evaluable cycles excluded those in which no intercourse occurred, or back-up contraception was used unless a pregnancy occurred in that cycle.

Women enrolled in the study provided 12,493 evaluable 28-day cycle equivalents in the first year and 27,115 evaluable cycles over the three-year treatment period. The PI for Year 1 was based on 9 pregnancies and the cumulative 3-year pregnancy rate was based on 22 pregnancies that occurred after the onset of treatment and within 7 days after Miudella removal or expulsion.

Table 4 shows the calculated annual pregnancy rates and cumulative 3-year pregnancy rate estimated by Pearl Index.

Table 4: Pearl Indices by Year and 3-Year Cumulative Pregnancy Rate [Of the 22 pregnancies, 2 occurred within 7 days of in-clinic removal of Miudella.]
Miudella Clinical Trial | Pearl Index |  |  | Cumulative 3-Year Pearl Index
Miudella Clinical Trial | Year 1 | Year 2 | Year 3 | Cumulative 3-Year Pearl Index
Number of Evaluable 28- day Cycles of Exposure | 12,493 | 8,150 | 6,472 | 27,115
Pregnancy Rate (95% Confidence Interval) | 0.94 (0.43,1.78) | 1.60 (0.76, 2.93) | 0.60 (0.12, 1.76) | 1.05 (0.66, 1.60)

Of 54 subjects who desired pregnancy after study discontinuation and provided follow-up information, approximately 74.1% conceived within 12 months after removal of Miudella. The majority of these subjects conceived within 4 months of removal and as early as the first week post-removal, demonstrating the reversibility of Miudella.

16 HOW SUPPLIED/STORAGE AND HANDLING

Miudella (copper intrauterine system) is a copper-containing sterile IUS preloaded in a single use inserter. Each single-use unit is packaged in a sealed tray with lid (NDC-82686-300-01). The IUS is comprised of a nitinol frame with 10 copper sleeves attached to provide a total copper surface area of 175mm^2, and a monofilament polymer retrieval thread tied to the vertical arm.

STORAGE AND HANDLING

Store at 20°C to 25°C (68°F to 77°F); excursions permitted between 15°C to 30°C (59°F to 86°F) [see USP Controlled Room Temperature].

17 PATIENT COUNSELING INFORMATION

Advise the patient to read the FDA-approved patient labeling (Patient Information).

Before inserting Miudella, counsel patients on the following:

Sexually Transmitted Infections: Advise patients that Miudella does not protect against HIV infection and other sexually transmitted infections.

Ectopic Pregnancy: Advise patients to report pregnancies and be evaluated immediately, as a pregnancy with Miudella in place is more likely to be an ectopic pregnancy, and the risks of ectopic pregnancy include the loss of fertility [See Warnings and Precautions (5.3)].

Intrauterine Pregnancy: Advise the patient to contact her healthcare provider if she thinks she might be pregnant. Inform the patient about the risks of intrauterine pregnancy while using Miudella, including the risks of leaving Miudella in place and the risks of removing Miudella or probing of the uterus. An intrauterine pregnancy with Miudella in place may result in septic abortion, with septicemia, septic shock, and possible death. Septic abortion typically requires hospitalization and treatment with intravenous antibiotics. Septic abortion may result in spontaneous abortion or a medical indication for pregnancy termination. A hysterectomy may be required if severe infection of the uterus occurs, which will result in permanent infertility.

If Miudella cannot be removed in a pregnant patient and remains in the uterus during a pregnancy, there is an increased risk of miscarriage, sepsis, premature labor and premature delivery. Advise patients that a pregnancy must be followed closely and advise patients to report immediately any symptom, such as flu- like symptoms, fever, chills, cramping, pain, bleeding, vaginal discharge or leaking of fluid, or any other symptom that suggests complications of the pregnancy. [See Warnings and Precautions (5.4)and Use in Special Populations (8.1)].

Sepsis: Advise the patient that severe infection or sepsis, including Group A streptococcal sepsis (GAS), can occur within the first few days after Miudella is inserted. Instruct her to contact a healthcare provider immediately if she develops severe pain or fever shortly after Miudella is inserted, as untreated sepsis can result in death [See Warnings and Precautions (5.5)].

Pelvic Infection: Advise the patient about the possibility of pelvic infections, including PID, after insertion of Miudella and that these infections can cause tubal damage leading to ectopic pregnancy or infertility, or infrequently can necessitate hysterectomy, or cause death. Teach patients to recognize and report to their healthcare provider promptly any symptoms of pelvic infection. These symptoms include development of menstrual disorders (spotting or prolonged or heavy bleeding), unusual vaginal discharge, abdominal or pelvic pain or tenderness, dyspareunia, chills, and fever. [See Warnings and Precautions (5.6)].

Perforation and Expulsion: Advise the patient that the IUS may be expelled from or perforate the uterus and instruct her on how she can check that the thread ends still protrude from the cervix. Inform her that excessive pain or vaginal bleeding during Miudella placement, worsening pain or bleeding after placement, or the inability to feel Miudella strings may occur with Miudella perforation and expulsion. Caution her not to pull on the thread ends and displace Miudella. Inform her that there is no contraceptive protection if Miudella is displaced (for example, expelled or perforated through the uterus). If perforation resulting in displacement occurs, Miudella will have to be located and removed; surgery may be required. Instruct the patient to contact her healthcare provider if she cannot feel the thread ends and to avoid intercourse or use a non-hormonal back-up birth control (such as condoms or spermicide) until the location of Miudella has been confirmed [See Warnings and Precautions (5.7, 5.8)].

Bleeding Pattern Alterations: Advise patients that heavier or longer periods and spotting between periods may occur. Instruct patients to report continued or severe symptoms to their healthcare provider [See Warnings and Precautions (5.10)].

Magnetic Resonance Imaging (MRI) Safety Information: Inform patients that Miudella can be safely scanned with MRI only under specific conditions. Instruct patients who will have an MRI to tell their healthcare provider that they have Miudella. [See Warnings and Precautions (5.11)].

Medical Diathermy: Instruct patients to tell their healthcare provider that they have Miudella prior to undergoing medical diathermy [see Warnings and Precautions (5.12)].

Clinical Considerations for Use and Removal:

1. Advise patients to contact their healthcare provider if any of the following occur:
  - Pelvic pain or pain during sex
  - Unusual vaginal discharge or genital sores
  - Possible exposure to STIs
  - Very heavy or prolonged vaginal bleeding
  - Missed period
2. Advise patients that they may use tampons or pads while using Miudella.
3. Advise patients that menstrual cups or discs are not recommended for use with Miudella. Use may cause Miudella to become displaced or expelled.

Manufactured for:
Sebela Women's Health Inc.
Roswell, GA 30076
www.miudella.com

PRINCIPAL DISPLAY PANEL - 175 mm Unit Tray Box

NDC 82686-300-01

Miudella
intrauterine copper contraceptive

Important: To be inserted in the uterus by a trained heathcare
provider by carefully following the insertion instructions.

Rx Only

ONE (1) STERILE UNIT: INTRAUTERINE USE

Contents: One (1) sterile packaged
system containing one intrauterine
copper contraceptive with approximately
175 mm^2of copper surface area,
preloaded in a single-use disposable
inserter. A Patient Information Booklet
is provided with each unit.

Ensure the Patient Information Booklet is
provided to the patient and review
contents prior to placement.

Insert MIUDELLA before the expiration
date printed on this box.